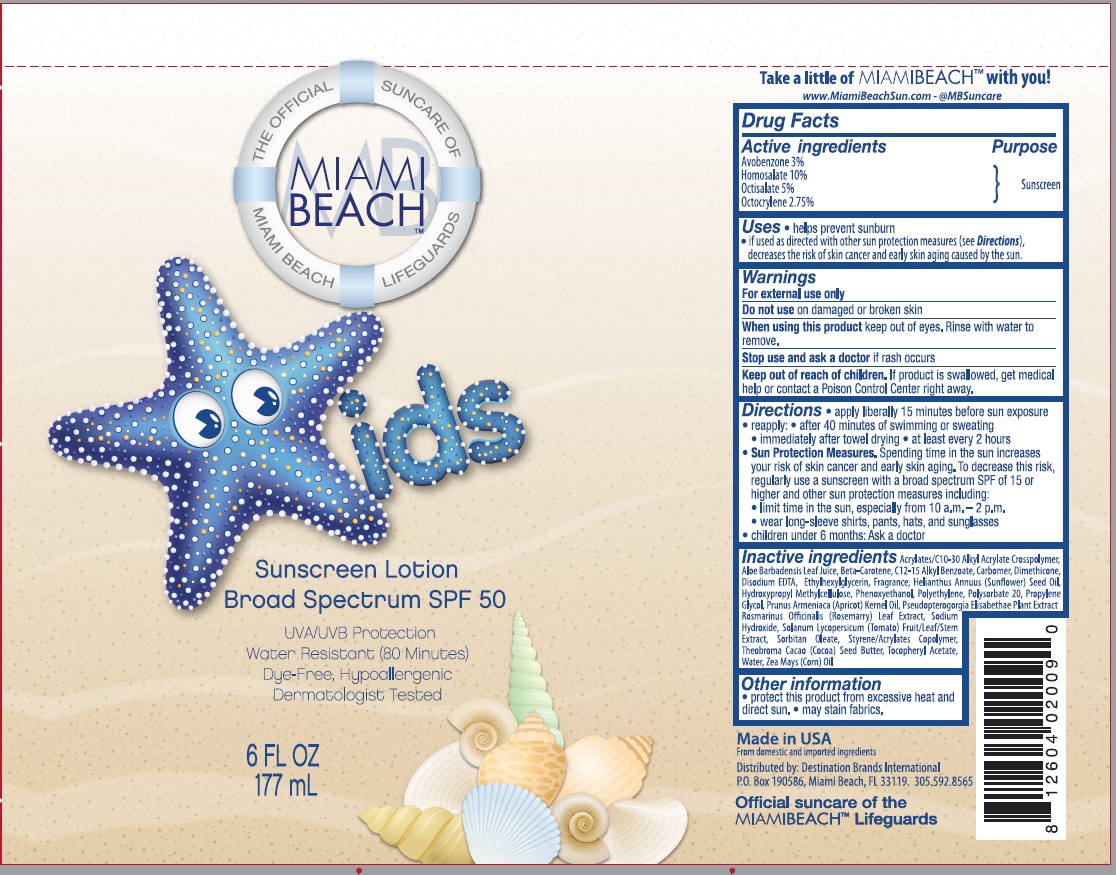 DRUG LABEL: Miami Beach
NDC: 58443-0256 | Form: LOTION
Manufacturer: Prime Enterprises Inc.
Category: otc | Type: HUMAN OTC DRUG LABEL
Date: 20200117

ACTIVE INGREDIENTS: AVOBENZONE 29.76 mg/1 mL; OCTISALATE 49.6 mg/1 mL; OCTOCRYLENE 27.28 mg/1 mL; HOMOSALATE 99.2 mg/1 mL
INACTIVE INGREDIENTS: COCOA BUTTER; .ALPHA.-TOCOPHEROL ACETATE; BUTYL METHACRYLATE/METHYL METHACRYLATE/METHACRYLIC ACID/STYRENE CROSSPOLYMER; SORBITAN MONOOLEATE; CARBOMER 1342; ALOE VERA LEAF; ALKYL (C12-15) BENZOATE; CARBOMER HOMOPOLYMER TYPE C (ALLYL PENTAERYTHRITOL CROSSLINKED); DIMETHICONE; EDETATE DISODIUM; SUNFLOWER OIL; CORN OIL; .BETA.-CAROTENE; HYPROMELLOSE, UNSPECIFIED; PHENOXYETHANOL; ETHYLHEXYLGLYCERIN; HIGH DENSITY POLYETHYLENE; POLYSORBATE 20; PROPYLENE GLYCOL; WATER; PSEUDOPTEROGORGIA ELISABETHAE; APRICOT KERNEL OIL; SOLANUM LYCOPERSICUM FRUITING TOP; ROSEMARY; SODIUM HYDROXIDE

Miami Beach Kids Sunscreen Lotion Broad Spectrum SPF 50

Active ingredients

Avobenzone 3%

Homosalate 10%

Octisalate 5%

Octocrylene 2.75%

Purpose

Sunscreen

Uses

• helps prevent sunburn

• if used as directed with other sun protection measures (see Directions), decreases the risk of skin cancer and early skin aging caused by the sun.

Warnings

For external use only

Do not use on damaged or broken skin

When using this product keep out of eyes. Rinse with water to remove.

Stop use and ask a doctor if rash occurs

Keep out of reach of children. If product is swallowed, get medical help or contact a Poison Control Center right away.

Directions

• apply liberally 15 minutes before sun exposure

• reapply: • after 40 minutes of swimming or sweating

• immediately after towel drying • at least every 2 hours

• Sun Protection Measures. Spending time in the sun increases your risk of skin cancer and early skin aging. To decrease this risk, regularly use a sunscreen with broad spectrum SPF of 15 or higher and other sun protection measures including:

• limit time in the sun, especially from 10 a.m. – 2 p.m.

• wear long-sleeve shirts, pants, hats, and sunglasses

• children under 6 months: Ask a doctor

Inactive ingredients

Acrylates/C10-30 Alkyl Acrylate Crosspolymer, Aloe Barbadensis Leaf Juice, Beta-Carotene, C12-15 Alkyl Benzoate, Carbomer, Dimethicone, Disodium EDTA, Ethylhexylglycerin, Fragrance, Helianthus Annuus (Sunflower) Seed Oil, Hydroxypropyl Methylcellulose, Phenoxyethanol, Polyethylene, Polysorbate 20, Propylene Glycol, Prunus Armeniaca (Apricot) Kernel Oil, Pseudopterogorgia Elisabethae Plant Extract, Rosmarinus Officinalis (Rosemarry) Leaf Extract, Sodium Hydroxide, Solanum Lycopersicum (Tomato) Fruit/Leaf/Stem Extract, Sorbitan Oleate, Styrene/Acrylates Copolymer, Theobroma Cacao (Cocoa) Seed Butter, Tocopheryl Acetate, Water, Zea Mays (Corn) Oil

Other information

• protect this product from excessive heat and direct sun. • may stain fabrics.